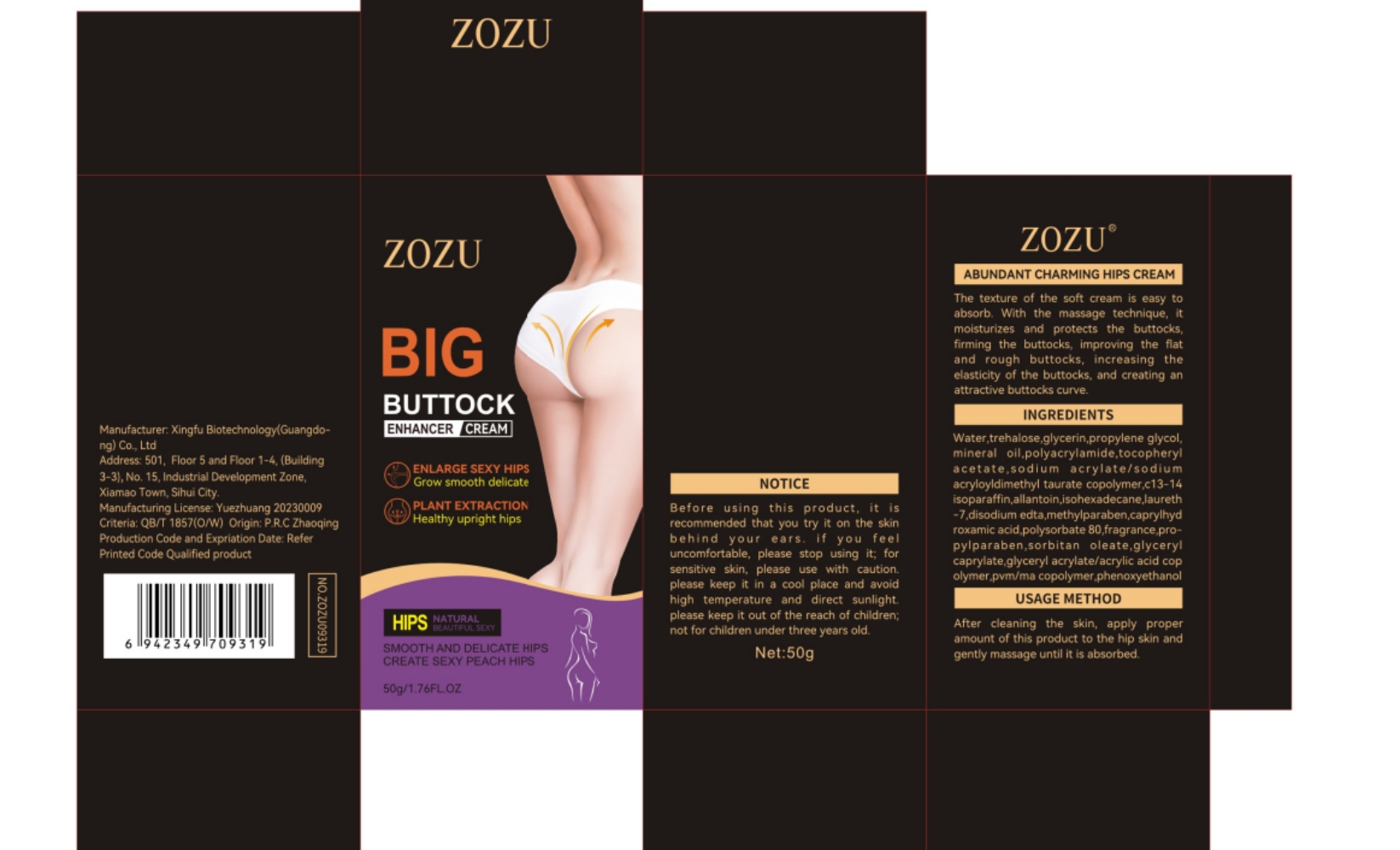 DRUG LABEL: zozu abundant charming hips cream
NDC: 84372-046 | Form: LOTION
Manufacturer: Shenzhen Zhumeng Times Technology Co., Ltd.
Category: otc | Type: HUMAN OTC DRUG LABEL
Date: 20240904

ACTIVE INGREDIENTS: TREHALOSE 5 g/50 g
INACTIVE INGREDIENTS: TAURINE; SORBITAN MONOOLEATE; POLYACRYLAMIDE (1500 MW); .ALPHA.-TOCOPHEROL ACETATE; FRAGRANCE MINT ORC2000774; GLYCERYL CAPRYLATE; GLATIRAMER ACETATE; ISOHEXADECANE; GLYCERIN; SODIUM; MINERAL OIL; ACRYLATE/ISOBUTYL METHACRYLATE/N-TERT-OCTYLACRYLAMIDE COPOLYMER (75000 MW); LAURETH-7; EDETATE DISODIUM; POLYSORBATE 80; GLYCERYL ACRYLATE/ACRYLIC ACID COPOLYMER (300000 CP AT 2%); METHYLPARABEN; PHENOL; ALLANTOIN; PARAFFIN; PROPYLENE GLYCOL; WATER; METHYL VINYL ETHER AND MALEIC ANHYDRIDE COPOLYMER (220000 WAMW); CAPRYLHYDROXAMIC ACID

Active ingredients

trehalose 5&

Purpose

The texture of the soft cream is easy to
absorb. With the massage technique,it
moisturizes and protects the buttocks,
firming the buttoeks,improving the fat
and rough buttoeks, inereasing the
clastieity of the buttoeks, and creating an
attractive buttocks curve

Uses

After cleaning the skin, appy proper
amount of this produet to the hip skin and
genty massage untl it is absorbed

Warnings

Before using this product, it is
reeommerded that you try it on the skin
behind your ears. if you feel
uneonfortable, please stop uing it fo
sensitive skin, please use with caution
please keep it in a cool place and avoid
high temperature and direct sunlight
please keep it out of the reach of children;
not for ehidren under three years old

Dosage and administration

For external use only.

Do not use

Before using this product, it is
reeommerded that you try it on the skin
behind your ears. if you feel
uneonfortable, please stop uing it fo
sensitive skin, please use with caution
please keep it in a cool place and avoid
high temperature and direct sunlight
please keep it out of the reach of children;
not for ehidren under three years old

When using section

After cleaning the skin, appy proper
amount of this produet to the hip skin and
genty massage untl it is absorbed

stop use

Broken or inflamed body

Keep out of reach of children.

If sxralowed, get medical help or contact a Poison Conirol Cenler ngiht away.

Inactive ingredients

Water,glycerin,propylene glycol,

mineral oil.polyacrylamide,tocopheryl

acetate,sodium acrylate/sodium

aeryloyldimethyl taurate copolymerc13-14

oparaffin,allantoin isohexadecane laureth

-7,disodium cdta,methylparaben,caprylhyd

roxamic acid polysorbate B0 fragrance pro-

pylparaben,sorbitan oleate,glyceryl

caprylate,glyceryl acrylate/acrylic acid cop

oyner pvm/ma copoymer phenoryethand